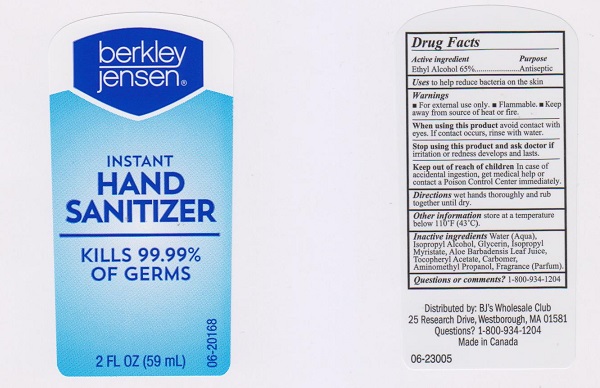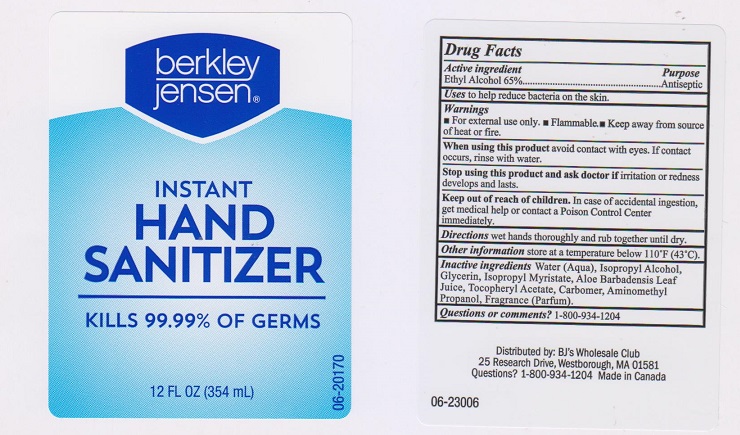 DRUG LABEL: Berkley Jensen
NDC: 68391-167 | Form: LIQUID
Manufacturer: BJWC
Category: otc | Type: HUMAN OTC DRUG LABEL
Date: 20170731

ACTIVE INGREDIENTS: ALCOHOL 650 mg/1 mL
INACTIVE INGREDIENTS: WATER; ISOPROPYL ALCOHOL; GLYCERIN; CARBOMER 934; AMINOMETHYLPROPANOL; ISOPROPYL MYRISTATE; ALOE VERA LEAF; .ALPHA.-TOCOPHEROL ACETATE, DL-

Drug Facts

Active ingredient

Ethyl Alcohol 65%

Purpose

Antiseptic

Uses

to help reduce bacteria on the skin.

Warnings

- for external use only
- flammable
- keep away from source of heat or fire

When using this product

avoid contact with eyes. If contact occurs, rinse with water.

Stop using this product and ask doctor if

irritation or redness develops and lasts.

Keep out of reach of children.

In case of accidental ingestion, get medical help or contact a Poison Control Center immediately.

Directions

wet hands thoroughly and rub together until dry.

Other information

store at a temperature below 110°F (43°C)

Inactive ingredients

Water (Aqua), Isopropyl Alcohol, Glycerin, Isopropyl Myristate, Aloe Barbadensis Leaf Juice, Tocopheryl Acetate, Carbomer, Aminomethyl Propanol, Fragrance (Parfum).

Questions or comments?

1-800-934-1204